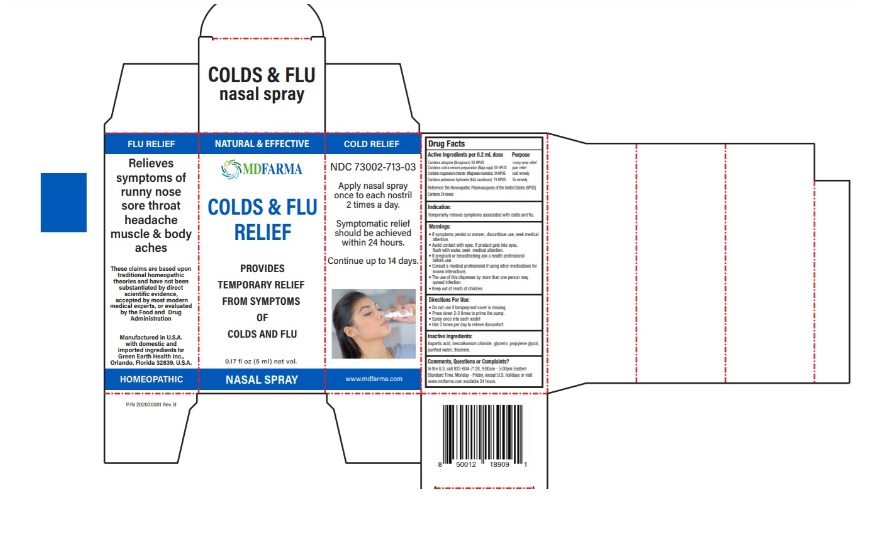 DRUG LABEL: MDFARMA COLD and FLU RELIEF
NDC: 73002-713 | Form: SPRAY
Manufacturer: Green Earth Health Inc.
Category: otc | Type: HUMAN OTC DRUG LABEL
Date: 20250722

ACTIVE INGREDIENTS: ATROPINE 5 [hp_X]/0.2 mL; NAJA NAJA VENOM 5 [hp_X]/0.2 mL; MAGNESIUM CHLORIDE 5 [hp_X]/0.2 mL; POTASSIUM HYDROXIDE 7 [hp_X]/0.2 mL
INACTIVE INGREDIENTS: ASPARTIC ACID; BENZALKONIUM CHLORIDE; GLYCERIN; PROPYLENE GLYCOL; WATER; THIAMINE

Active Ingredient

Active ingredient Purpose

Contains atropine (Atropinum) 5X HPUS …………………………………....... runny nose relief
Contains cobra venom preparation (Naja naja) 5X HPUS ………..... pain relief
Contains magnesium chloride (Magnesia muriatica) 5X HPUS….... cold remedy
Contains potassium hydroxide (Kali causticum) 7X HPUS ………. .... flu remedy
Reference: the Homeopathic Pharmacopoeia of the United States (HPUS)

Contains 24 doses

Use

Temporarily relieves symptoms associated with colds and flu.

Warnings

If symptoms persist or worsen, discontinue use, seek medical attention.
• Avoid contact with eyes. If product gets into eyes, flush with water, seek medical attention.
• If pregnant or breastfeeding ask a health professional before use.
• Consult a medical professional if using other medications for known interactions.
• The use of this dispenser by more than one person may spread infection.

Keep out of reach of children.

Directions

- Do not use if tamperproof cover is missing.
- Press down 2-3 times to prime the pump.
- Spray once into each nostril
- Use 2 times per day to relieve discomfort.

Inactive ingredients

Aspartic acid, benzalkonium chloride, glycerin, propylene glycol, purified water, thiamine.

Comments, Questions or Complaints?

In the U.S. call 833-604-7128, 9:00am - 5:00pm Eastern Standard Time, Monday - Friday, except U.S. holidays or visit www.mdfarma.com available 24 hours.